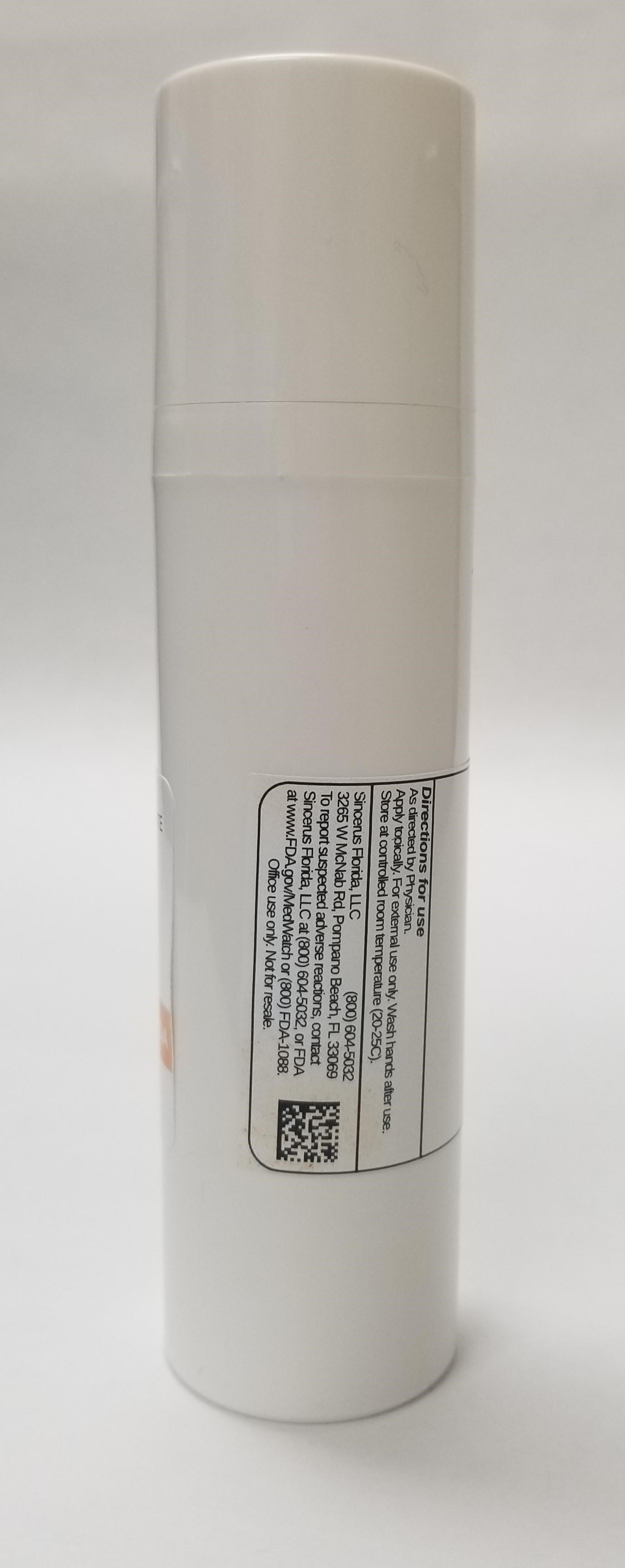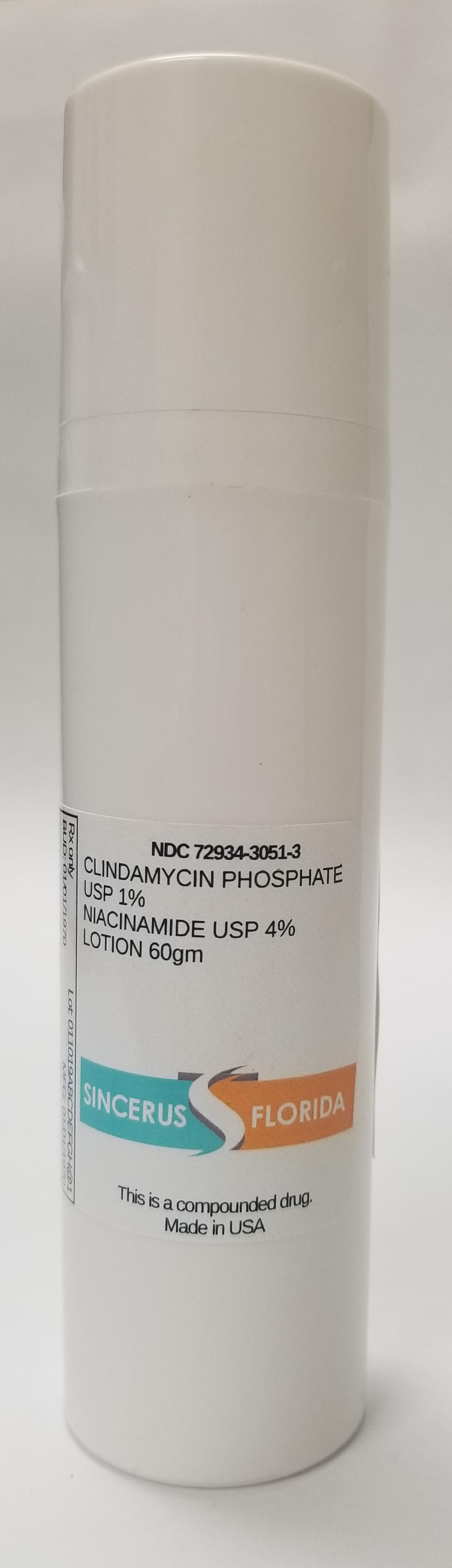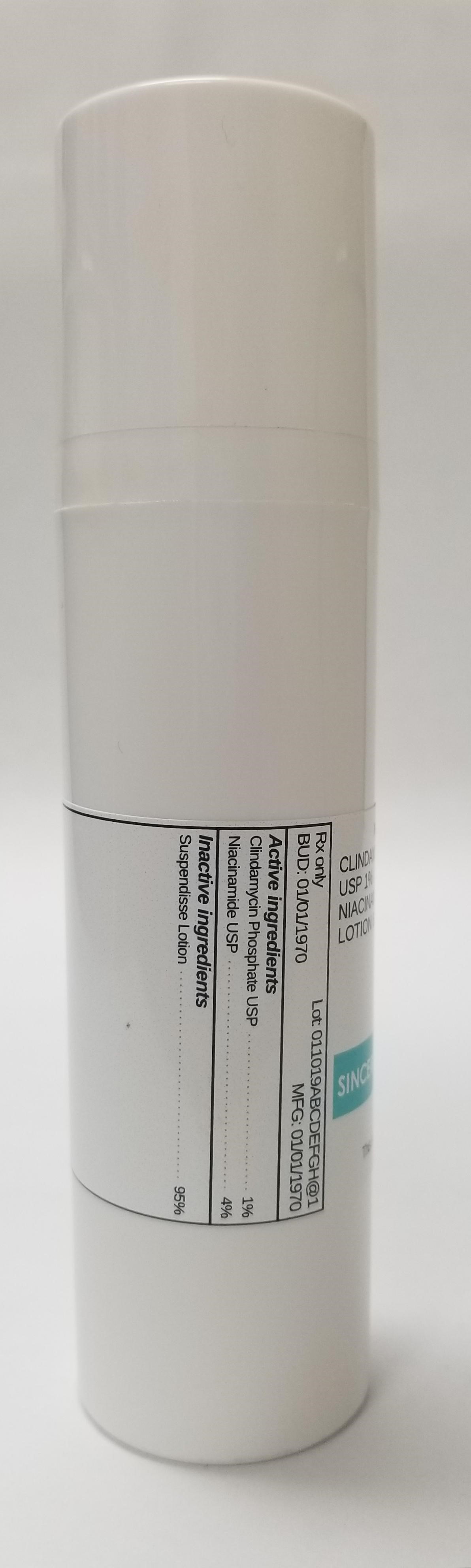 DRUG LABEL: CLINDAMYCIN 1% / NIACINAMIDE 4%
NDC: 72934-3051 | Form: LOTION
Manufacturer: Sincerus Florida, LLC
Category: prescription | Type: HUMAN PRESCRIPTION DRUG LABEL
Date: 20190423

ACTIVE INGREDIENTS: CLINDAMYCIN PHOSPHATE 1 g/100 g; NIACINAMIDE 4 g/100 g

CLINDAMYCIN 1% / NIACINAMIDE 4%